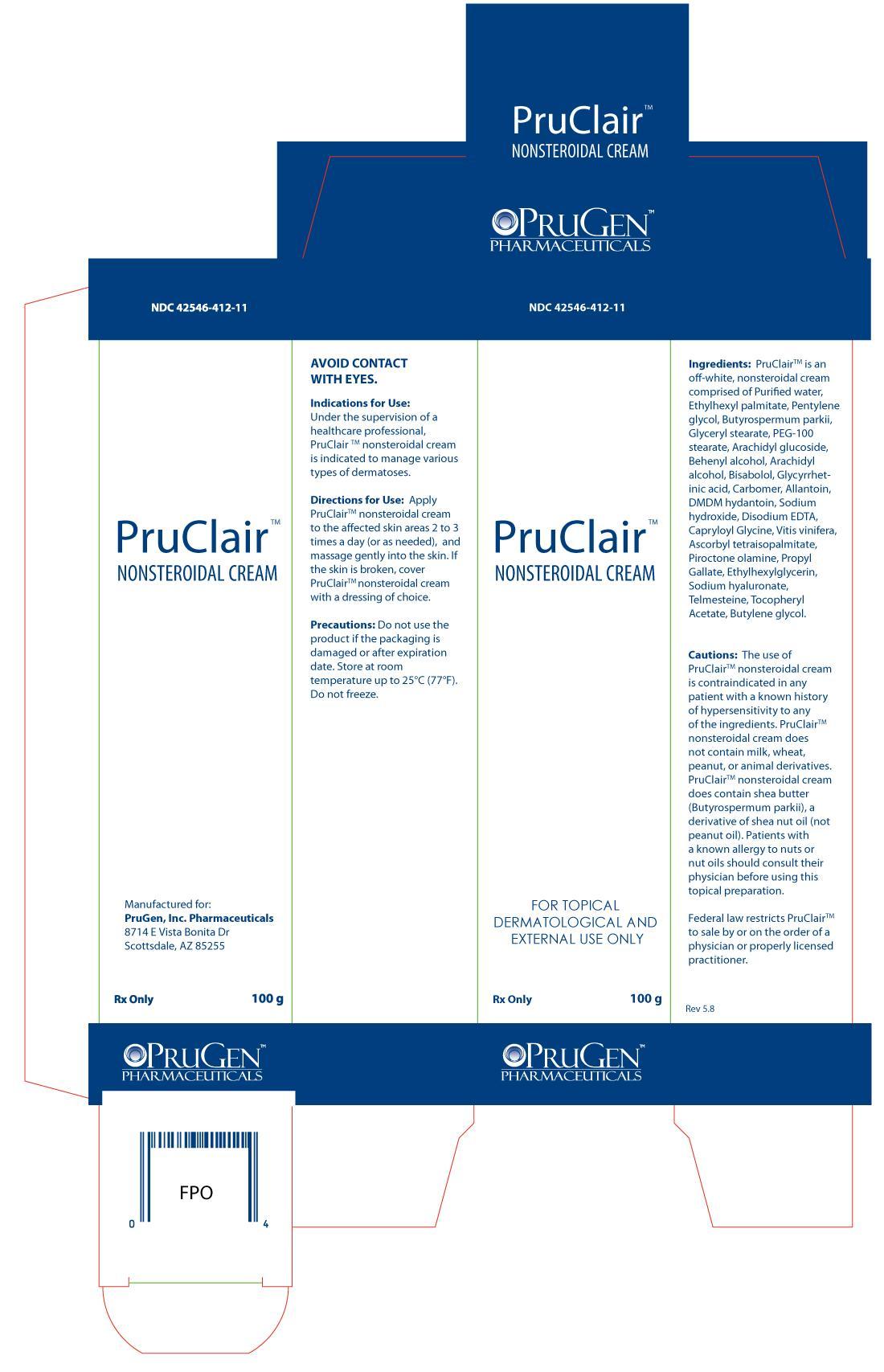 DRUG LABEL: PruClair
NDC: 42546-412
Manufacturer: PruGen, Inc.
Category: other | Type: PRESCRIPTION MEDICAL DEVICE LABEL
Date: 20120904

PruClair Nonsteroidal Cream

INDICATIONS & USAGE

Under the supervision of a healthcare professional, PruClair nonsteroidal cream is indicated to manage various types of dermatoses.

DIRECTIONS FOR USE:

Apply PruClair nonsteroidal cream to the affected skin areas 2 to 3 times a day (or as needed), and massage gently into the skin. If the skin is broken, cover PruClair nonsteroidal cream with a dressing of choice.

INGREDIENTS

PruClair is an off-white, nonsteroidal cream comprised of Purified water, Ethylhexyl palmitate, Pentylene glycol, Butyrospermum parkii, Glyceryl stearate, PEG-100 stearate, Arachidyl glucoside, Behenyl alcohol, Arachidyl alcohol, Bisabolol, Glycyrrhetinic acid, Carbomer, Allantoin, DMDM hydantoin, Sodium hydroxide, Disodium EDTA, Capryloyl Glycine, Vitis vinifera, Ascorbyl tetraisopalmitate, Piroctone olamine, Propyl Gallate, Ethylhexylglycerin, Sodium hyaluronate, Telmesteine, Tocopheryl Acetate, Butylene glycol.

CAUTIONS

PruClair nonsteroidal cream does not contain milk, wheat, peanut, or animal derivatives. PruClair nonsteroidal cream does contain shea butter (Butyrospermum parkii), a derivative of shea nut oil (not peanut oil). Patients with a known allergy to nuts or nut oils should consult their doctor before using this topical preparation.

Do not use the product if the packaging is damaged or after expiration date. Store at room temperature up to 25°C (77°F). Do not freeze.

OTHER PATIENT INFORMATION

The formulation contains no dyes or fragrances and is well tolerated and safe for patients of all ages. PruClair nonsteroidal cream does not contain milk, wheat or animal derivatives.

HOW SUPPLIED

100g tube (NDC 42546-412-11)

Manufactured for:
PruGen, Inc. Pharmaceuticals
8714 E Vista Bonita Dr
Scottsdale, AZ 85255

PruClair Carton Label

NDC 42546-412-11

PruClair Nonsteroidal Cream

For Topical Dermatological and External Use Only

Rx Only

100g

PruGen, Inc. Pharmaceuticals